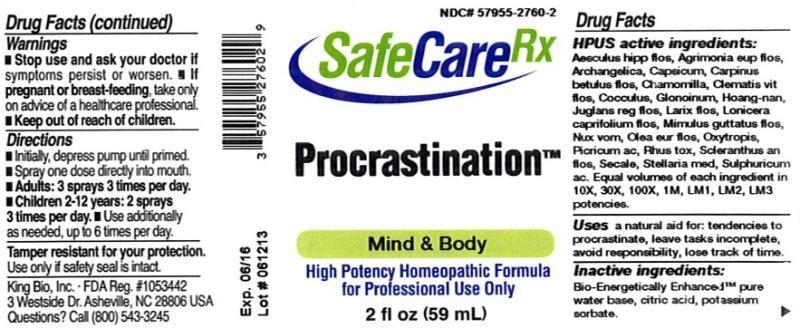 DRUG LABEL: Procrastination
NDC: 57955-2760 | Form: LIQUID
Manufacturer: King Bio Inc.
Category: homeopathic | Type: HUMAN OTC DRUG LABEL
Date: 20130812

ACTIVE INGREDIENTS: AESCULUS HIPPOCASTANUM FLOWER 10 [hp_X]/59 mL; AGRIMONIA EUPATORIA FLOWER 10 [hp_X]/59 mL; ANGELICA ARCHANGELICA ROOT 10 [hp_X]/59 mL; CAPSICUM 10 [hp_X]/59 mL; CARPINUS BETULUS FLOWERING TOP 10 [hp_X]/59 mL; MATRICARIA RECUTITA 10 [hp_X]/59 mL; CLEMATIS VITALBA FLOWER 10 [hp_X]/59 mL; ANAMIRTA COCCULUS SEED 10 [hp_X]/59 mL; NITROGLYCERIN 10 [hp_X]/59 mL; STRYCHNOS WALLICHIANA BARK 10 [hp_X]/59 mL; JUGLANS REGIA FLOWERING TOP 10 [hp_X]/59 mL; LARIX DECIDUA FLOWERING TOP 10 [hp_X]/59 mL; LONICERA CAPRIFOLIUM FLOWERING TOP 10 [hp_X]/59 mL; MIMULUS GUTTATUS FLOWERING TOP 10 [hp_X]/59 mL; STRYCHNOS NUX-VOMICA SEED 10 [hp_X]/59 mL; OLEA EUROPAEA FLOWER 10 [hp_X]/59 mL; OXYTROPIS LAMBERTII TOP 10 [hp_X]/59 mL; PICRIC ACID 10 [hp_X]/59 mL; TOXICODENDRON PUBESCENS LEAF 10 [hp_X]/59 mL; SCLERANTHUS ANNUUS FLOWERING TOP 10 [hp_X]/59 mL; CLAVICEPS PURPUREA SCLEROTIUM 10 [hp_X]/59 mL; STELLARIA MEDIA 10 [hp_X]/59 mL; SULFURIC ACID 10 [hp_X]/59 mL
INACTIVE INGREDIENTS: WATER; CITRIC ACID MONOHYDRATE; POTASSIUM SORBATE

Procrastination

Drug Facts

___________________________________________________________________________________________________________________

HPUS active ingredients: Aesculus hippocastanum, flos, Agrimonia eupatoria, flos, Angelica archangelica, Capsicum annuum, Carpinus betulus, flos, Chamomilla, Clematis vitalba, flos, Cocculus indicus, Glonoinum, Hoang-nan, Juglans regia, flos, Larix decidua, flos, Lonicera caprifolium, flos, Mimulus guttatus, flos, Nux vomica, Olea europaea, flos, Oxytropis lambertii, Picricum acidum, Rhus toxicodendron, Scleranthus annuus, flos, Secale cornatum, Stellaria media, Sulphuricum acidum. Equal volumes of each ingredient in 10X, 30X, 100X,1M, LM1, LM2, LM3 potencies.

INDICATIONS AND USAGE

Uses a natural aid for: tendencies to procrastinate, leave tasks incomplete, avoid responsibility, lose track of time.

INACTIVE INGREDIENT

Inactive ingredients: Bio-Energetically Enhanced™ pure water base, citric acid, potassium sorbate.

Warnings

- Stop use and ask your doctor if symptoms persist or worsen.
- If pregnant or breast-feeding, take only on advice of a healthcare professional.

- Keep out of reach of children.

Directions

- Initially, depress pump until primed.
- Spray one dose directly into mouth.
- Adults: 3 sprays 3 times per day.
- Children 2-12 years: 2 sprays 3 times per day.
- Use additionally as needed, up to 6 times per day.

OTHER SAFETY INFORMATION

Tamper resistant for your protection. Use only if safety seal is intact.

PURPOSE

Use a natural aid for:

- tendencies to procrastinate
- leave tasks incomplete
- avoid responsibility
- lose track of time.